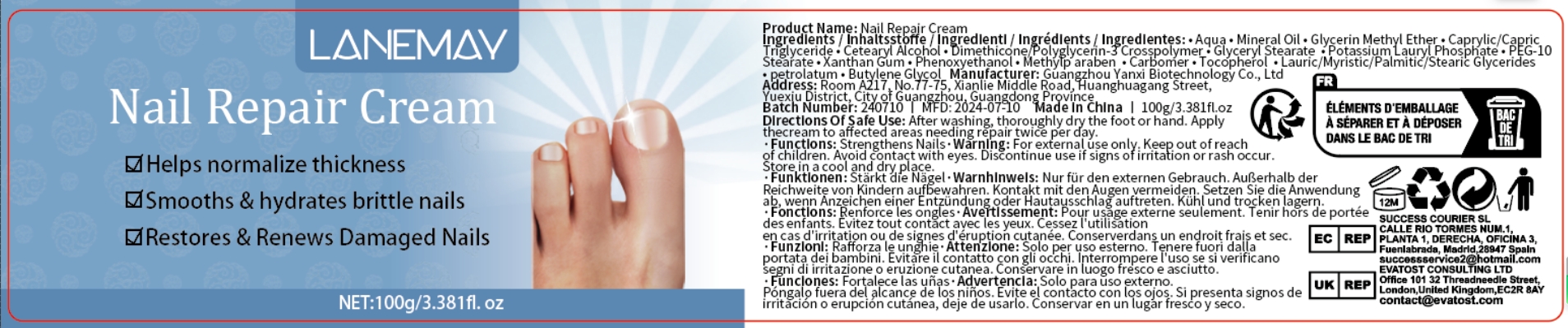 DRUG LABEL: Nail Repair Cream
NDC: 84025-069 | Form: CREAM
Manufacturer: Guangzhou Yanxi Biotechnology Co., Ltd
Category: otc | Type: HUMAN OTC DRUG LABEL
Date: 20240718

ACTIVE INGREDIENTS: MINERAL OIL 5 mg/100 mL; GLYCERIN METHYL ETHER 3 mg/100 mL
INACTIVE INGREDIENTS: WATER

DOSAGE AND ADMINISTRATION

USE AS A NORMAL HAIR CREAM

WARNINGS

keep out of children

INACTIVE INGREDIENT

Aqua

INDICATIONS AND USAGE

For daity hair care

keep out of children

PURPOSE

strong and nourishing hair